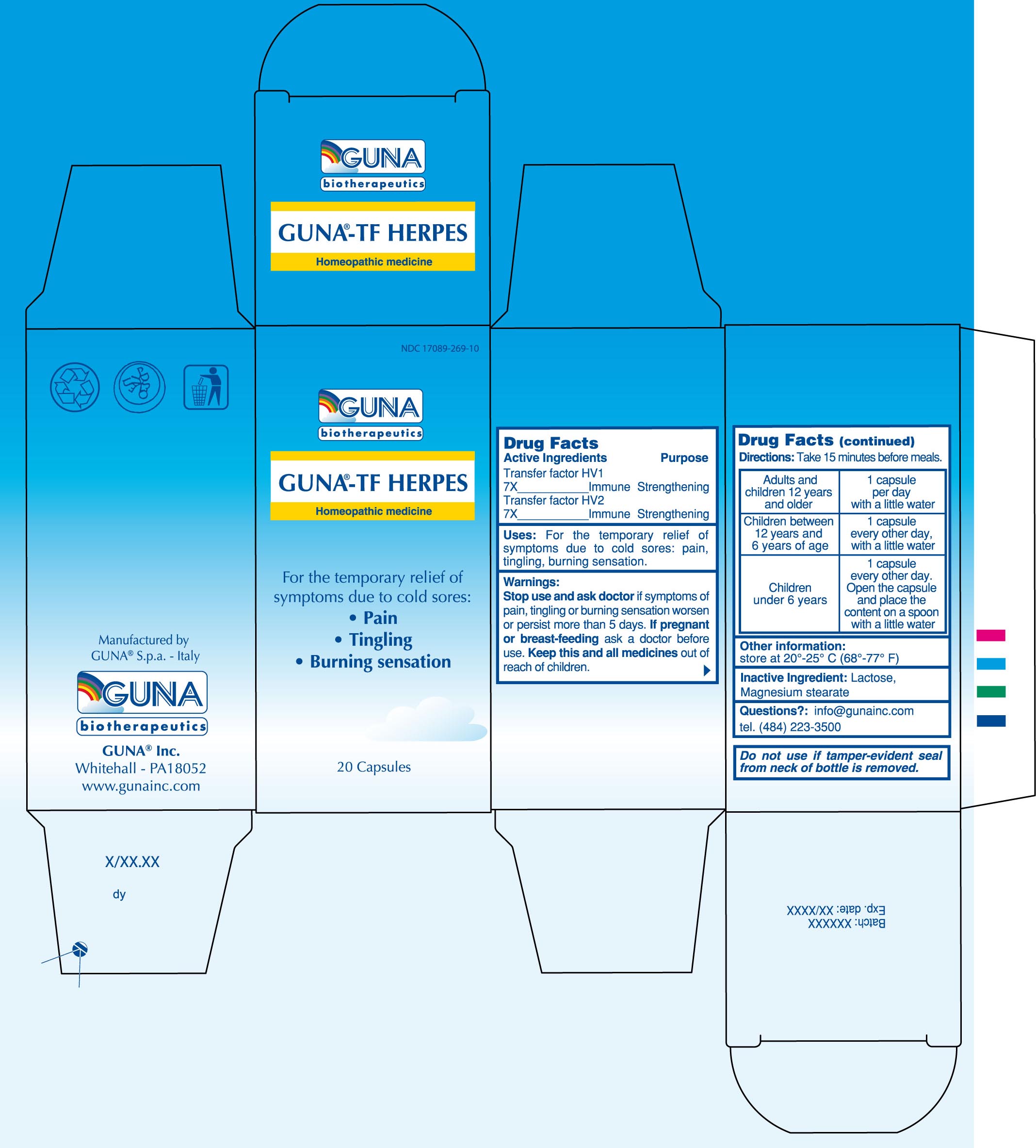 DRUG LABEL: GUNA-TF HERPES
NDC: 17089-269 | Form: CAPSULE, GELATIN COATED
Manufacturer: Guna spa
Category: homeopathic | Type: HUMAN OTC DRUG LABEL
Date: 20100331

ACTIVE INGREDIENTS: HUMAN HERPESVIRUS 1 7 [hp_X]/4600 mg; HUMAN HERPESVIRUS 2 7 [hp_X]/4600 mg
INACTIVE INGREDIENTS: LACTOSE 4048 mg/4600 mg; MAGNESIUM STEARATE 92 mg/4600 mg

DRUG FACTS

ACTIVE INGREDIENTS/PURPOSE

TRANSFER FACTOR HV1 7X IMMUNE STRENGTHENING
TRANSFER FACTOR HV2 7X IMMUNE STRENGTHENING

USES

For the temporary relief of symptoms due to cold sores: pain, tingling, burning sensation.

WARNINGS

Stop use and ask doctor if symptoms of tingling or burning sensation worsen or persist more than 5 days

PREGNANCY

If pregnant or breast-feeding ask a doctor before use

WARNINGS

Keep this and all medicines out of reach of children

DIRECTIONS

Take 15 minutes before meals
Adults and children 12 years and older 1 capsule per day with a little water
Children between 12 years and 6 years of age 1 capsule every other day, with a little water
Children under 6 years 1 capsule every other day. Open the capsule and place the content on a spoon with a little water

QUESTIONS

Questions?: info@gunainc.com
Tel. (484) 223-3500